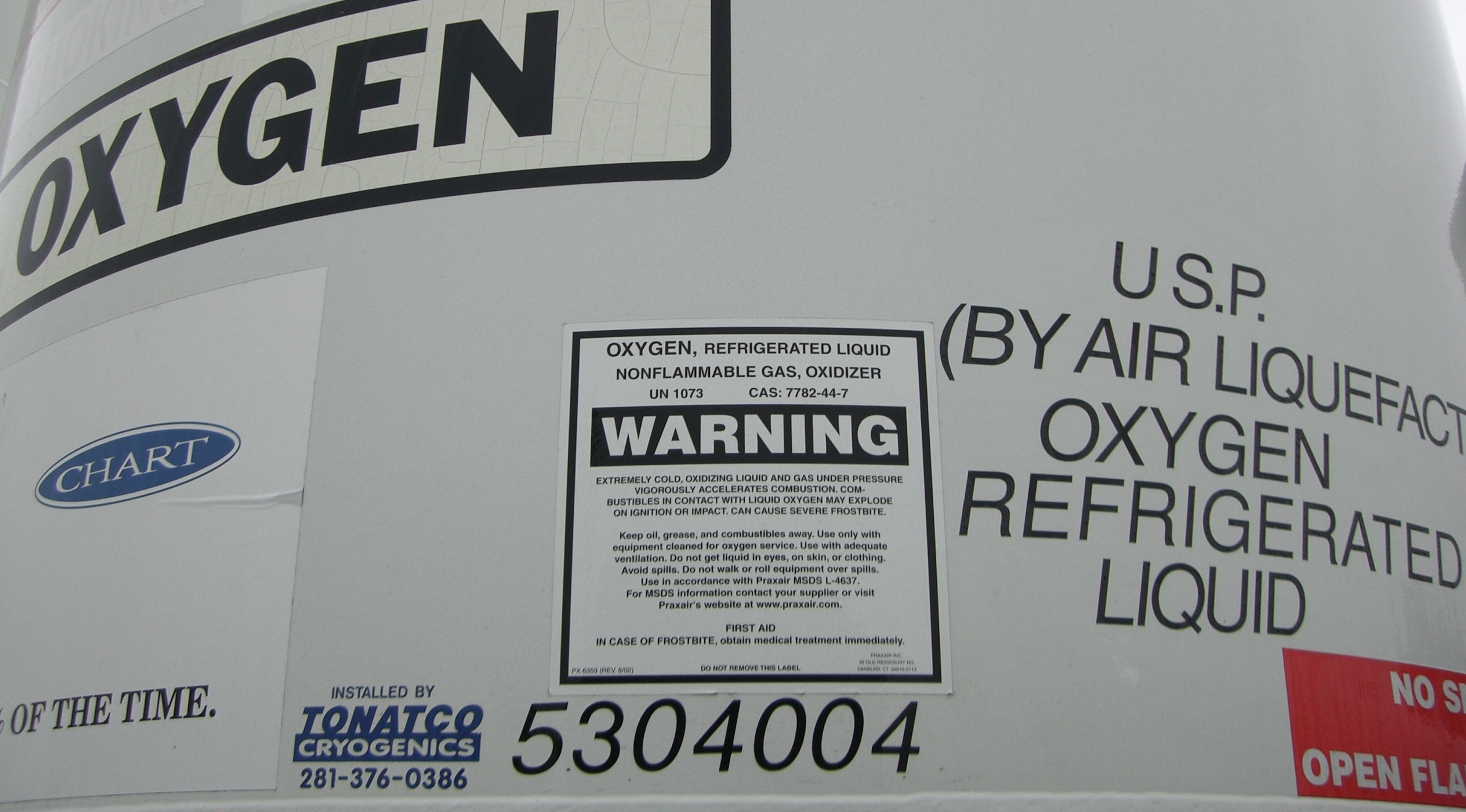 DRUG LABEL: Oxygen
NDC: 15062-003 | Form: GAS
Manufacturer: Texas Welders Supply Company
Category: prescription | Type: HUMAN PRESCRIPTION DRUG LABEL
Date: 20101217

ACTIVE INGREDIENTS: Oxygen 996 mL/1 L

Oxygen

PACKAGE LABEL

OXYGEN
CHART % OF THE TIME
INSTALLED BY TONATCO CRYOGENCIS
281-376-0386
5304004
US.P.
(BY AIR LIQUEFACTION
OXYGEN REFRIGERATED LIQUIDE
NO SMOKING OR OPEN FLAMES
Oxygen, Refrigerated Liquid Nonflammable Gas, Oxidizer UN 1073 CAS: 7782-44-7
WARNING
EXTREMELY COLD, OXIDIZING LIQUID AND GAS UNDER PRESSURE VIROROUSLY ACCELERATES COMBUSTION. COMBUSTIBLES IN CONTACT WITH LIQUID OXYGEN MAY EXPLODE ON IGNITION OR IMPACT. CAN CAUSE SEVERE FROSTBITE.
KEEP OIL, GREASE, AND COMBUSTIBLES AWAY. USE ONLY WITH EQUIPMENT CLEANED FOR OXYGEN SERVICE. USE WITH ADEQUATE VENTILATION. DO NOT GET LIQUID IN EYES, SKIN, OR CLOTHING. AVOID SPILLS. DO NOT WALK OR ROLL EQUIPMENT OVER SPILLS. USE IN ACCORDANCE WITH PRAXAIR MSDS L-4637. FOR MSDS INFORMATION CONTACT YOUR SUPPLIER OR VISIT PRAXAIR'S WEBSITE AAT WWW.PRAXAIR.COM
FIRST AID
IN CASE OF FROSTBITE, OBTAIN MEDICAL TREATMENT IMMEDIATELY.
PX 6359 (REV. 8/02)
DO NOT REMOVE THIS LABEL
PRAXAIR INC.
39 OLD RIDGEBURY ROAD
DANBURY, CT 06810